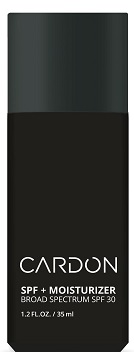 DRUG LABEL: Cardon
NDC: 72475-001 | Form: LOTION
Manufacturer: Cardon, Inc
Category: otc | Type: HUMAN OTC DRUG LABEL
Date: 20251226

ACTIVE INGREDIENTS: HOMOSALATE 7 g/100 mL; OCTISALATE 4.3 g/100 mL; AVOBENZONE 2.5 g/100 mL
INACTIVE INGREDIENTS: CARBOMER HOMOPOLYMER, UNSPECIFIED TYPE; AMMONIUM ACRYLOYLDIMETHYLTAURATE, DIMETHYLACRYLAMIDE, LAURYL METHACRYLATE AND LAURETH-4 METHACRYLATE COPOLYMER, TRIMETHYLOLPROPANE TRIACRYLATE CROSSLINKED (45000 MPA.S); ETHYLHEXYLGLYCERIN; HYDROXYETHYL ACRYLATE/SODIUM ACRYLOYLDIMETHYL TAURATE COPOLYMER (45000 MPA.S AT 1%); TROMETHAMINE; ISOHEXADECANE; HOUTTUYNIA CORDATA WHOLE; TERT-BUTYL ALCOHOL; SODIUM ACRYLATE/SODIUM ACRYLOYLDIMETHYLTAURATE COPOLYMER (4000000 MW); DOCOSANOL; XANTHAN GUM; TURMERIC; PORTULACA OLERACEA WHOLE; CENTELLA ASIATICA; SALVIA HISPANICA SEED; OPUNTIA FICUS-INDICA STEM; WATER; PROPANEDIOL; BUTYLENE GLYCOL; 1,2-HEXANEDIOL; STYRENE/ACRYLAMIDE COPOLYMER (MW 500000); PHENOXYETHANOL; PENTYLENE GLYCOL; INVERT SUGAR; EDETATE DISODIUM; OXYGEN; BUTYLOCTYL SALICYLATE; ETHYLHEXYL METHOXYCRYLENE; POLY(METHYL METHACRYLATE; 450000 MW); GLYCERIN

CARDON SPF + MOISTURIZER

Drug Facts

Active ingredients

Avobenzone 2.5%

Homosalate 7.0%

Octyl salicylate 4.3%

Purpose

Sunscreen

Uses

- helps prevent sunburn
- if used as directed with other sun protection measures (see Directions), decreases the risk of skin cancer and early skin aging caused by the sun

Warnings

- For external use only

- Do not useon damaged or broken skin

WHEN USING

- When using this productkeep out of eyes. Rinse with water to remove.

- Stop use and ask a doctorif rash occurs.

- Keep out of reach of children.If product is swallowed, get medical help or contact a Poison Control Center right away.

Directions

- For Sunscreen Use:apply liberally 15 minutes before sun exposure
- reapply at least every 2 hours
- use a water resistant sunscreen if swimming or sweating
- Sun Protection Measures:Spending time in the sun increases your risk of skin cancer and early skin aging. To decrease this risk, regularly use a sunscreen with a Broad Spectrum SPF of 15 or higher and other sun protection measures including:
- limit time in the sun, especially from 10 a.m. - 2 p.m.
- wear long-sleeve shirts, pants, hats and sunglasses
- Children under 6 months; Ask a doctor

Other information

- protect this product from excessive heat and direct sun

Other information

- protect this product from excessive heat and direct sun

INACTIVE INGREDIENT

Inactive ingredientswater, propanediol, butyloctyl salicylate, ethylhexyl methoxycrylene, polymethyl methacrylate, butylene glycol, 1,2-hexanediol, styrene/acrylates copolymer, phenoxyethanol, fragrance, glycerin, pentylene glycol, saccharide hydrolysate, sodium acrylate/sodiumacryloyldimethyl taurate copolymer, carbomer, polyacrylate crosspolymer-6, behenyl alcohol, ethylhexyglycerin, hydroxyethyl acrylate/sodiumacryloyldimethyl taurate copolymer, tromethamine, xanthan gum, isohexadecane, curcuma longa (turmeric) root extract, portulaca oleracea extract, centella asiatica extract, houttuynia cordata extract, salvia hispanica seed extract, opuntia ficus-indica stem extract, t-butyl alcohol, disodium edta, oxygen

Distributed by Cardon Inc, NY, NY 10004 USA

Made in Korea

PACKAGE LABEL

CARDON

SPF + MOISTURIZER

BROAD SPECTRUM SPF 30

1.2 FL.OZ. / 35 ml